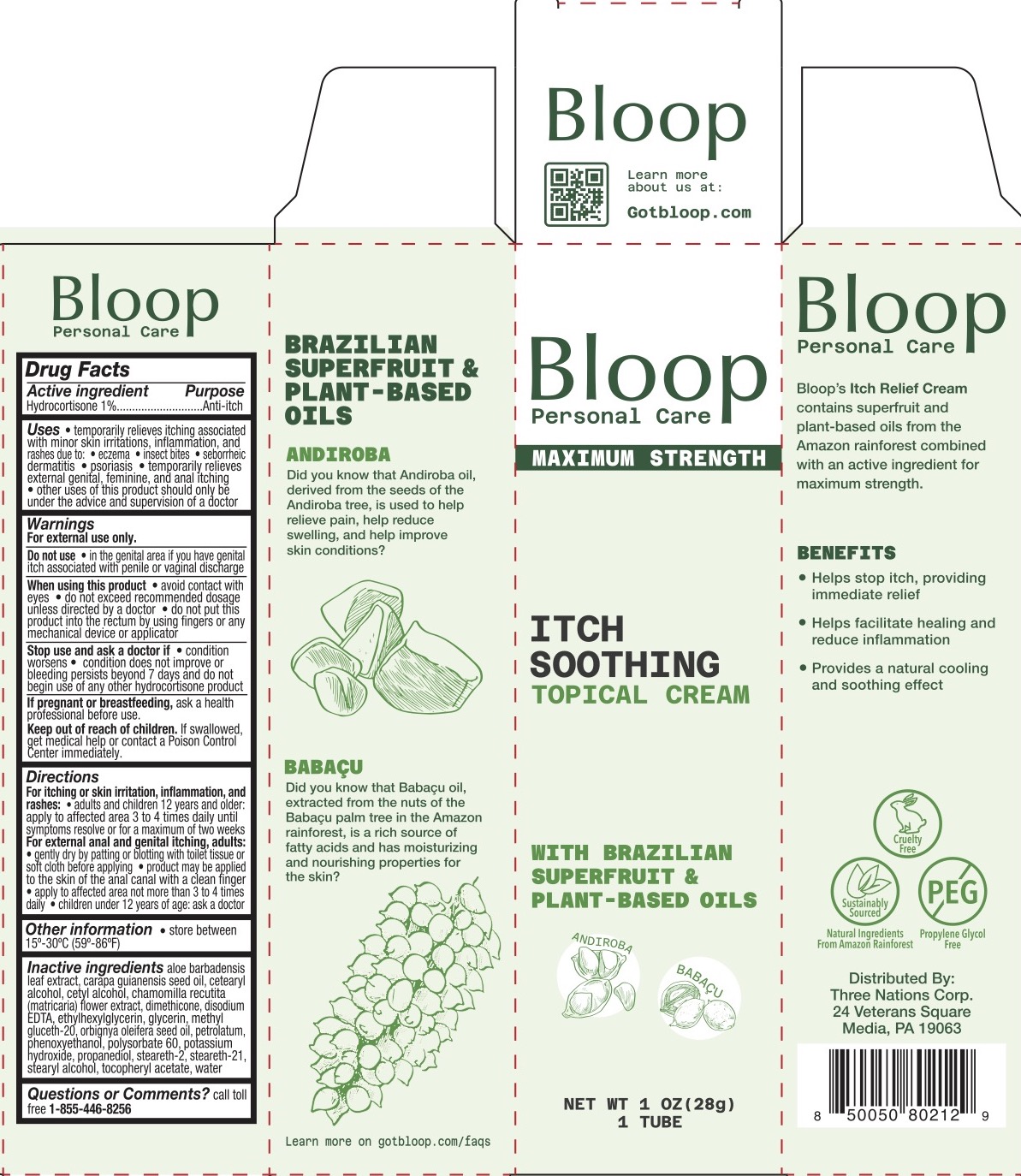 DRUG LABEL: Bloop Itch Soothing Topical
NDC: 83838-415 | Form: CREAM
Manufacturer: Three Nations Corp
Category: otc | Type: HUMAN OTC DRUG LABEL
Date: 20231130

ACTIVE INGREDIENTS: HYDROCORTISONE 1 g/100 g
INACTIVE INGREDIENTS: POLYSORBATE 60; STEARETH-21; BABASSU OIL; POTASSIUM HYDROXIDE; PETROLATUM; ALOE VERA LEAF; CARAPA GUIANENSIS SEED OIL; CETOSTEARYL ALCOHOL; CETYL ALCOHOL; EDETATE DISODIUM; CHAMOMILE; PROPANEDIOL; DIMETHICONE 200; ETHYLHEXYLGLYCERIN; GLYCERIN; .ALPHA.-TOCOPHEROL ACETATE; WATER; METHYL GLUCETH-20; PHENOXYETHANOL; STEARETH-2; STEARYL ALCOHOL

Bloop Itch Soothing Topical Cream

ACTIVE INGREDIENT

Hydrocortisone 1%

PURPOSE

Anti-itch

INDICATIONS AND USAGE

- Temporarily relieves itching associated with minor skin irritations, inflammation, and rashes due to:
- eczema
- insect bites
- seborrheic dermatitiss
- psoriasis
- Temporarily relieves external genital, feminine, and anal itching
- Other uses of this product should only be under the advice and supervision of a doctor

WARNINGS

For external use only.

Do not use

- in the genital area if you have genital itch associated with penile or vaginal discharge

When using this product

- avoid contact with eyes
- do not exceed recommended dosage unless directed by a doctor
- do not put this product into the rectum by using fingers or any mechanical device or applicator

Stop use and ask a doctor if

- condition worsens
- condition does not improve within 7 days or bleeding persists beyond 7 days and do not begin use of any other hydrocortisone product.

PREGNANCY OR BREAST FEEDING

Ask a health professional before use.

KEEP OUT OF REACH OF CHILDREN

If swallowed, get medical help or contact a Poison Control Center immediately.

DOSAGE AND ADMINISTRATION

For itching or skin irritation, inflammation, and rashes:

- Adults and children 12 years and older: apply to the affected area 3 to 4 times daily until symptoms resolve or for a maximum of two weeks.

For external anal and genital itching adults:

- gently dry by patting or blotting with toilet tissue or soft cloth before applying
- product may be applied to the skin of the anal canal with a clean finger
- apply to affected area not more than 3 to 4 times daily
- Children under 12 years of age consult a doctor

INACTIVE INGREDIENT

Aloe barbadensis leaf extract, carapa guianensis seed oil, cetearyl alcohol, cetyl alcohol, chamomilla recutita (matricaria) flower extract, dimethicone, disodium EDTA, ethylhexylglycerin, glycerin, methyl gluceth-20, orbignya oleifera seed oil, petrolatum, phenoxyethanol, polysorbate 60, potassium hydroxide, propanediol, steareth-2, steareth-21, stearyl alcohol, tocopheryl acetate, water